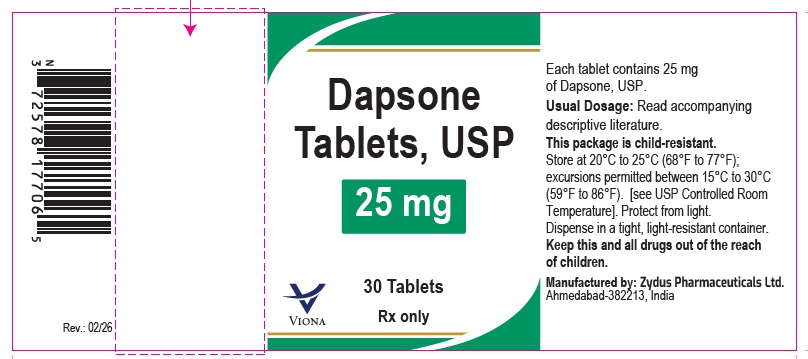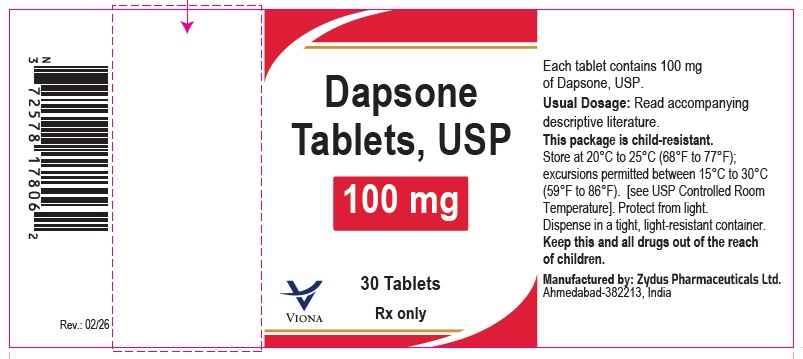 DRUG LABEL: Dapsone
NDC: 70771-1979 | Form: TABLET
Manufacturer: Zydus Lifesciences Limited
Category: prescription | Type: HUMAN PRESCRIPTION DRUG LABEL
Date: 20260227

ACTIVE INGREDIENTS: DAPSONE 25 mg/1 1
INACTIVE INGREDIENTS: MICROCRYSTALLINE CELLULOSE; CROSCARMELLOSE SODIUM; HYDROXYPROPYL CELLULOSE, UNSPECIFIED; SILICON DIOXIDE; MAGNESIUM STEARATE

Dapsone Tablets, USP

PACKAGE LABEL.PRINCIPAL DISPLAY PANEL

NDC 70771-1979-3 in bottle of 30 tablets

Dapsone Tablets USP, 25 mg

Rx only

30 tablets

NDC 70771-1980-3 in bottle of 30 tablets

Dapsone Tablets USP, 100 mg

Rx only

30 tablets